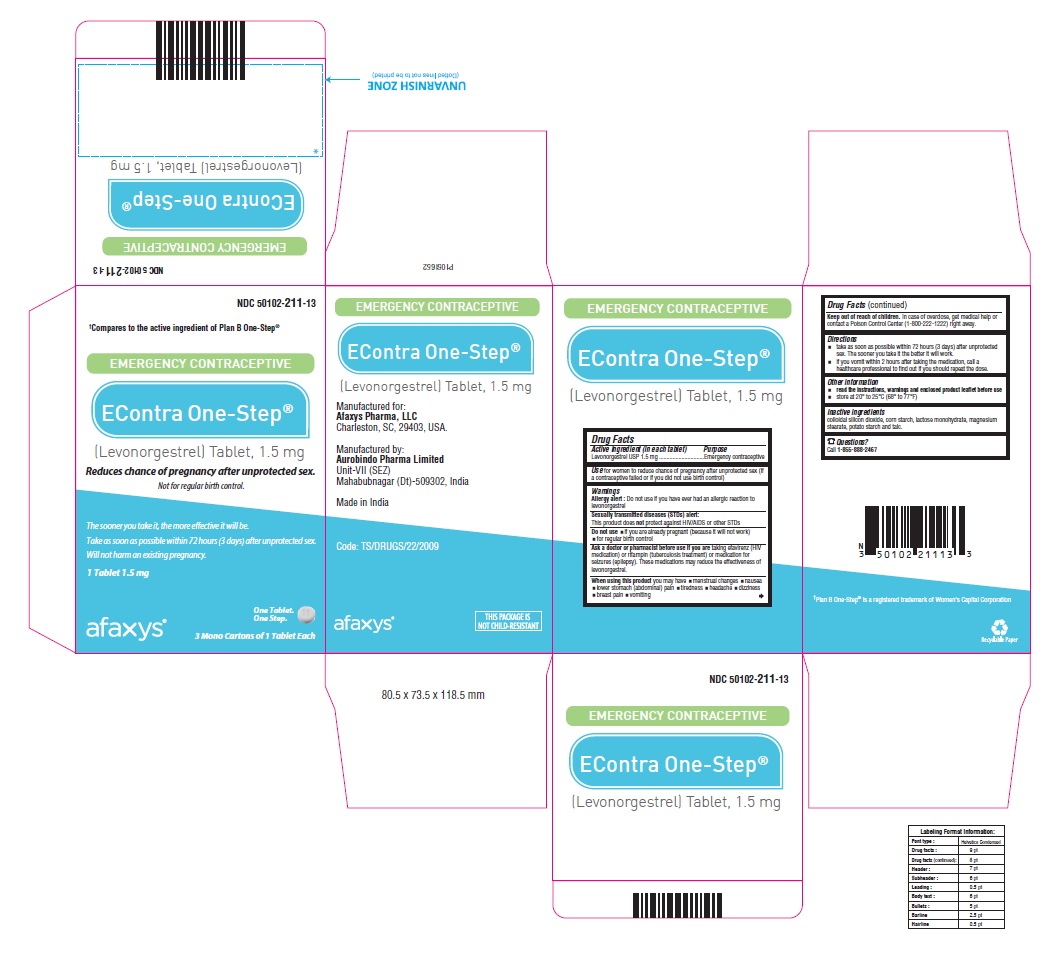 DRUG LABEL: EContra One-Step
NDC: 50102-211 | Form: TABLET
Manufacturer: Afaxys Pharma, LLC
Category: otc | Type: Human OTC Drug Label
Date: 20250408

ACTIVE INGREDIENTS: LEVONORGESTREL 1.5 mg/1 1
INACTIVE INGREDIENTS: SILICON DIOXIDE; STARCH, CORN; LACTOSE MONOHYDRATE; MAGNESIUM STEARATE; STARCH, POTATO; TALC

EContra One-Step®
(Levonorgestrel) Tablet 1.5 mg

Drug Facts

Active ingredient (in each tablet)
Levonorgestrel 1.5 mg

Purpose

Emergency contraceptive

Use

for women to reduce chance of pregnancy after unprotected sex (if a contraceptive failed or if you did not use birth control)

Warnings

Allergy alert: Do not use if you have ever had an allergic reaction to levonorgestrel
Sexually transmitted diseases (STDs) alert: This product does not protect against HIV/AIDS or other STDs

Do not use

- if you are already pregnant (because it will not work)
- for regular birth control

Ask a doctor or pharmacist before use if you are

taking efavirenz (HIV medication) or rifampin (tuberculosis treatment) or medication for seizures (epilepsy). These medications may reduce the effectiveness of levonorgestrel.

When using this product you may have

- menstrual changes
- nausea
- lower stomach (abdominal) pain
- tiredness
- headache
- dizziness
- breast pain
- vomiting

Keep out of reach of children.

In case of overdose, get medical help or contact a Poison Control Center (1-800-222-1222) right away.

Directions

- take as soon as possible within 72 hours (3 days) after unprotected sex. The sooner you take it the better it will work.
- if you vomit within 2 hours after taking the medication, call a healthcare professional to find out if you should repeat the dose.

Other information

- read the instructions, warnings and enclosed product leaflet before use
- do not use if carton is open or seal is removed
- store at 20° to 25°C (68° to 77°F)

Inactive ingredients

colloidal silicon dioxide, corn starch, lactose monohydrate, magnesium stearate, potato starch and talc.

Questions?

Call 1-855-888-2467
Manufactured for:
Afaxys Pharma, LLC
Charleston, SC, 29403, USA
Manufactured by:
Aurobindo Pharma Limited
Unit-VII (SEZ)
Mahabubnagar (Dt)-509302, India
Made in India
Code: TS/DRUGS/22/2009

Patient Information

EContra One-Step®
(Levonorgestrel) Tablet, 1.5 mg
Emergency Contraceptive
One Tablet. One Step.
What You Need to Know
What is EContra One-Step®?
EContra One-Step®is emergency contraception that helps prevent pregnancy after birth control failure or unprotected sex. It is a backup method of preventing pregnancy and should not be used as regular birth control.
What EContra One-Step® is not.
EContra One-Step® will not work if you are already pregnant and will not affect an existing pregnancy. EContra One-Step® will not protect you from HIV infection (the virus that causes AIDS) and other sexually transmitted diseases (STDs).
When should I use EContra One-Step®?
The sooner you take emergency contraception, the better it works. You should use EContra One-Step® within 72 hours (3 days) after you have had unprotected sex.
EContra One-Step® is a backup or emergency method of birth control you can use when:

- your regular birth control was used incorrectly or failed
- you did not use any birth control method

When not to use EContra One-Step®.
EContra One-Step® should not be used:

- as a regular birth control method, because it’s not as effective as regular birth control.
- if you are already pregnant, because it will not work.
- if you are allergic to levonorgestrel or any other ingredients in EContra One-Step®.

When should I talk to a doctor or pharmacist?

Ask a doctor or pharmacist before use if you are taking efavirenz (HIV medication) or rifampin (tuberculosis treatment) or medication for seizures (epilepsy). These medications may reduce the effectiveness of EContra One-Step® and increase your chance of becoming pregnant. Your doctor may prescribe another form of emergency contraception that may not be affected by these medications.
How does EContra One-Step® work?
EContra One-Step® works before release of an egg from the ovary. As a result, EContra One-Step® usually stops or delays the release of an egg from the ovary. EContra One-Step® is one tablet that contains a higher dose of levonorgestrel than birth control pills and works in a similar way to prevent pregnancy.
How can I get the best results from EContra One-Step®?
You have 72 hours (3 days) to try to prevent pregnancy after birth control failure or unprotected sex. The sooner you take EContra One-Step®, the better it works.
How effective is EContra One-Step®?
If EContra One-Step® is taken as directed, it can significantly decrease the chance that you will get pregnant. About 7 out of every 8 women who would have gotten pregnant will not become pregnant.
How will I know EContra One-Step® worked?
You will know EContra One-Step® has been effective when you get your next period, which should come at the expected time, or within a week of the expected time. If your period is delayed beyond 1 week, it is possible you may be pregnant. You should get a pregnancy test and follow up with your healthcare professional.
Will I experience any side effects?

- some women may have changes in their period, such as a period that is heavier or lighter or a period that is early or late. If your period is more than a week late, you may be pregnant.
- if you have severe abdominal pain, you may have an ectopic pregnancy, and should get immediate medical attention.
- when used as directed, EContra One-Step® is safe and effective. Side effects may include changes in your period, nausea, lower stomach (abdominal) pain, tiredness, headache, dizziness, and breast tenderness.
- if you vomit within 2 hours of taking the medication, call a healthcare professional to find out if you should repeat the dose.

What if I still have questions about EContra One-Step®?
If you have questions or need more information, call our toll-free number Afaxys Pharma, LLC at 1-855-888-2467.
Other Information
Keep out of reach of children:
In case of overdose, get medical help or contact a Poison Control Center right away at 1-800-222-1222.
Do not use if the blister seal is opened.
Store at room temperature 20° to 25°C (68° to 77°F).
Active ingredient: levonorgestrel 1.5 mg
Inactive ingredients: colloidal silicon dioxide, corn starch, lactose monohydrate, magnesium stearate, potato starch, and talc.
If you are sexually active, you should see a healthcare provider for routine checkups. Your healthcare provider will talk to you about and, if necessary, test you for sexually transmitted diseases, teach you about effective methods of routine birth control, and answer any other questions you may have.
Manufactured for:
Afaxys Pharma, LLC
Charleston, SC, 29403, USA.
Manufactured by:
Aurobindo Pharma Limited
Unit-VII (SEZ)
Mahabubnagar (Dt)-509302, India
Made in India
Code: TS/DRUGS/22/2009
Revised: 03/2023

PACKAGE LABEL-PRINCIPAL DISPLAY PANEL - 1.5 mg (3 Blister Carton Label)

†Compares to the active ingredient of Plan B One-Step®
NDC 50102-211-13
EMERGENCY CONTRACEPTIVE
EContra One-Step®
(Levonorgestrel) Tablet, 1.5 mg
Reduces chance of pregnancy after unprotected sex.
Not for regular birth control.
The sooner you take it, the more effective it will be.
Take as soon as possible within 72 hours (3 days) after unprotected sex.
Will not harm an existing pregnancy.
1 Tablet 1.5 mg
One Tablet.
One Step.
afaxys®
3 Mono Cartons of 1 Tablet Each